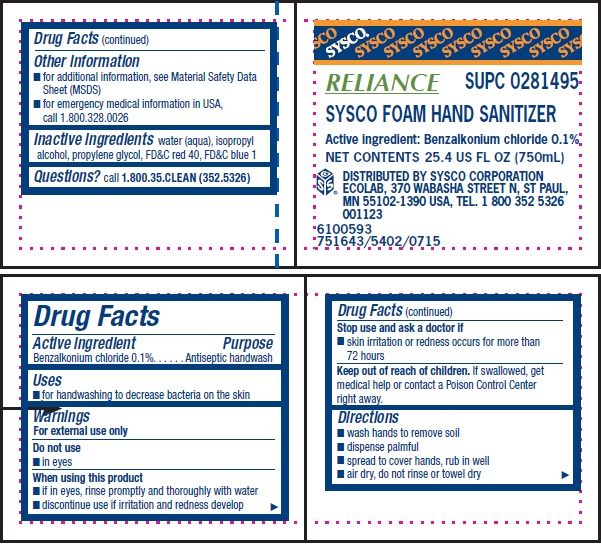 DRUG LABEL: Reliance Hand Saniziter
NDC: 47593-478 | Form: SOLUTION
Manufacturer: Ecolab Inc.
Category: otc | Type: HUMAN OTC DRUG LABEL
Date: 20240426

ACTIVE INGREDIENTS: BENZALKONIUM CHLORIDE 0.1 mg/100 mL
INACTIVE INGREDIENTS: WATER; ISOPROPYL ALCOHOL; PROPYLENE GLYCOL; FD&C RED NO. 40; FD&C BLUE NO. 1

Drug Facts

Active ingredient

Benzalkonium chloride 0.1%

Purpose

Antiseptic handwash

Uses

- for handwashing to decrease bacteria on the skin

Warnings

For external use only

Do not use

- in eyes

WHEN USING

- if in eyes, rinse promptly and thoroughly with water
- discontinue use if irritation and redness develop

Stop use and ask a doctor if

- skin irritation or redness occurs for more than 72 hours

KEEP OUT OF REACH OF CHILDREN

Keep our of reach of children. If swallowed, get medical help or contact a Poison Control Center right away.

Direction

- wash hands to remove soil
- dispense palmful
- spread to cover hands, rub in well
- air dry, do not rinse or towel dry

Other information

- for additional information, see Material Safety Data Sheet (MSDS)
- for emergency medical information in USA, call 1.800.328.0026

INACTIVE INGREDIENT

Inactive ingredients water (aqua), isopropyl alcohol, propylene glycol, FDC red 40, FDC blue 1

Questions? call 1.800.35.CLEAN (352.5326)

Principal display panel and representative label

SYSCO

RELIANCE SUPC 0281495

SYSCO FOAM HAND SANITIZER

Active ingredient: Benzalkonium chloride 0.1%

NET CONTENTS 25.4 US FL OZ (750mL)

DISTRIBUTED BY SYSCO CORPORATION

ECOLAB, 370 WABASHA STREET N, ST PAUL,

MN 55102-1390 USA, TEL. 1 800 352 5326

001123

6100593

751643/5402/0715